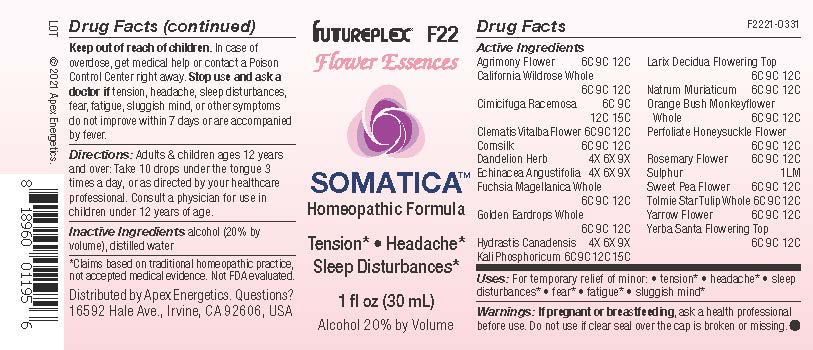 DRUG LABEL: F22
NDC: 63479-0622 | Form: SOLUTION/ DROPS
Manufacturer: Apex Energetics Inc.
Category: homeopathic | Type: HUMAN OTC DRUG LABEL
Date: 20240108

ACTIVE INGREDIENTS: ROSA CALIFORNICA WHOLE 12 [hp_C]/1 mL; ECHINACEA ANGUSTIFOLIA 9 [hp_X]/1 mL; LATHYRUS ODORATUS FLOWER 12 [hp_C]/1 mL; ACHILLEA MILLEFOLIUM FLOWER 12 [hp_C]/1 mL; FUCHSIA MAGELLANICA WHOLE 12 [hp_C]/1 mL; CORN SILK 12 [hp_C]/1 mL; TARAXACUM OFFICINALE FLOWERING TOP 9 [hp_X]/1 mL; EHRENDORFERIA CHRYSANTHA WHOLE 12 [hp_C]/1 mL; GOLDENSEAL 9 [hp_X]/1 mL; POTASSIUM PHOSPHATE, DIBASIC 15 [hp_C]/1 mL; LARIX DECIDUA FLOWERING TOP 12 [hp_C]/1 mL; SULFUR 1 [hp_Q]/1 mL; CALOCHORTUS TOLMIEI WHOLE 12 [hp_C]/1 mL; ERIODICTYON CALIFORNICUM FLOWERING TOP 12 [hp_C]/1 mL; BLACK COHOSH 15 [hp_C]/1 mL; DIPLACUS AURANTIACUS WHOLE 12 [hp_C]/1 mL; LONICERA CAPRIFOLIUM FLOWER 12 [hp_C]/1 mL; AGRIMONIA EUPATORIA FLOWER 12 [hp_C]/1 mL; SODIUM CHLORIDE 12 [hp_C]/1 mL; SALVIA ROSMARINUS FLOWER 12 [hp_C]/1 mL; CLEMATIS VITALBA FLOWER 12 [hp_C]/1 mL
INACTIVE INGREDIENTS: WATER; ALCOHOL

F22

Active Ingredients
Agrimony Flower | 6C 9C 12C
California Wildrose Whole | 6C 9C 12C
Cimicifuga Racemosa | 6C 9C 12C 15C
Clematis Vitalba Flower | 6C 9C 12C
Cornsilk | 6C 9C 12C
Dandelion Herb | 4X 6X 9X
Echinacea Angustifolia | 4X 6X 9X
Fuchsia Magellanica Whole | 6C 9C 12C
Golden Eardrops Whole | 6C 9C 12C
Hydrastis Canadensis | 4X 6X 9X
Kali Phosphoricum | 6C 9C 12C 15C
Larix Decidua Flowering Top | 6C 9C 12C
Natrum Muriaticum | 6C 9C 12C
Orange Bush Monkeyflower Whole | 6C 9C 12C
Perfoliate Honeysuckle Flower | 6C 9C 12C
Rosemary Flower | 6C 9C 12C
Sulphur | 1 LM
Sweet Pea Flower | 6C 9C 12C
Tolmie Star-Tulip Whole | 6C 9C 12C
Yarrow Flower | 6C 9C 12C
Yerba Santa Flowering Top | 6C 9C 12C

INDICATIONS AND USAGE

Uses:

For temporary relief of minor:

tension*

headache*

sleep disturbances*

fear*

fatigue*

sluggish mind*

*Claims based on traditional homeopathic practice, not accepted medical evidence. Not FDA evaluated.

Warnings:

PREGNANCY OR BREAST FEEDING

If pregnant or breastfeeding, ask a health professional before use.

Do not use if clear seal over the cap is broken or missing.

Keep out of reach of children. In case of overdose, get medical help or contact a Poison Control Center right away.

Stop use and ask a doctor if tension, headache, sleep disturbances, fear, fatigue, sluggish mind, or other symptoms do not improve within 7 days or are accompanied by fever.

Directions:

Adults & children ages 12 years and over: Take 10 drops under the tongue 3 times a day, or as directed by your healthcare professional. Consult a physician for use in children under 12 years of age.

Inactive Ingredients

alcohol (20% by volume), distilled water

Distributed by Apex Energetics. Questions?

16592 Hale Ave., Irvine, CA 92606, USA

PACKAGE LABEL

FUTUREPLEX® F22

Flower Essences

SOMATICA™

Homeopathic Formula

Tension*

Headache*

Sleep Disturbances*

1 fl oz (30 mL)

Alcohol 20% by Volume